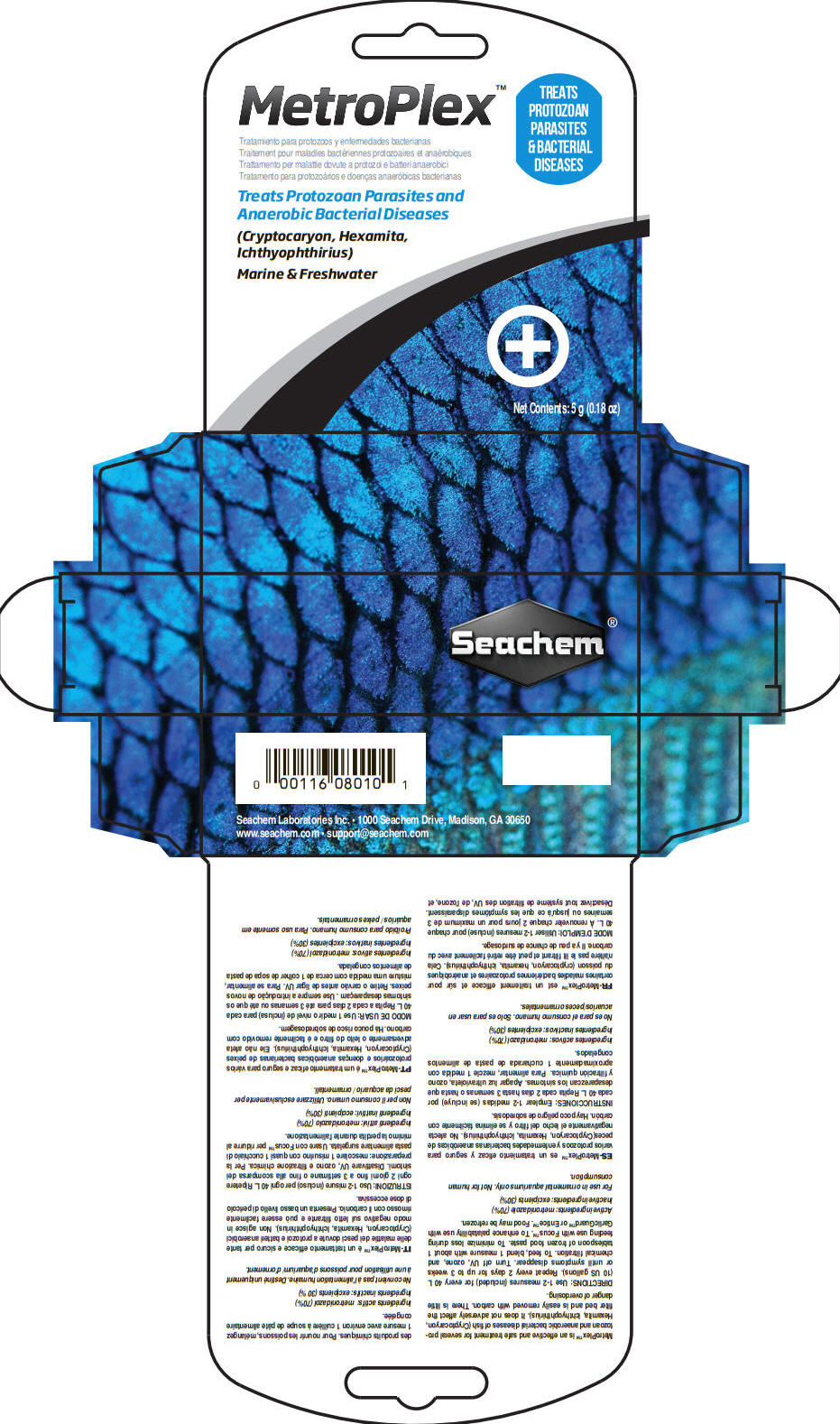 DRUG LABEL: Metroplex
NDC: 55999-081 | Form: POWDER
Manufacturer: Seachem Laboratories Inc.
Category: animal | Type: OTC ANIMAL DRUG LABEL
Date: 20180713

ACTIVE INGREDIENTS: Metronidazole 700 mg/1 g

Metroplex™

VETERINARY INDICATIONS

MetroPlex™ is an effective and safe treatment for several protozoan and anaerobic bacterial diseases of fish (Cryptocaryon, Hexamita, Ichthyophthirius). It does not adversely affect the filter bed and is easily removed with carbon. There is little danger of overdosing.

DOSAGE AND ADMINISTRATION

DIRECTIONS: Use 1-2 measures (included) for every 40 L (10 US gallons). Repeat every 2 days for up to 3 weeks or until symptoms disappear. Turn off UV, ozone, and chemical filtration. To feed, blend 1 measure with about 1 tablespoon of frozen food paste. To minimize loss during feeding use with Focus™. To enhance palatability use with GarlicGuard™ or Entice™. Food may be refrozen.

Active ingredients: metronidazole (70%)

Inactive ingredients: excipients (30%)

SAFE HANDLING WARNING

For use in ornamental aquariums only. Not for human consumption.

Seachem Laboratories Inc. • 1000 Seachem Drive, Madison, GA 30650

www.seachem.com • support@seachem.com

PRINCIPAL DISPLAY PANEL - 5 g Vial Carton

MetroPlex™

TREATS
PROTOZOAN
PARASITES
& BACTERIAL
DISEASES

Treats Protozoan Parasites and
Anaerobic Bacterial Diseases

(Cryptocaryon, Hexamita,
Ichthyophthirius)

Marine & Freshwater

Net Contents: 5 g (0.18 oz)

Seachem®